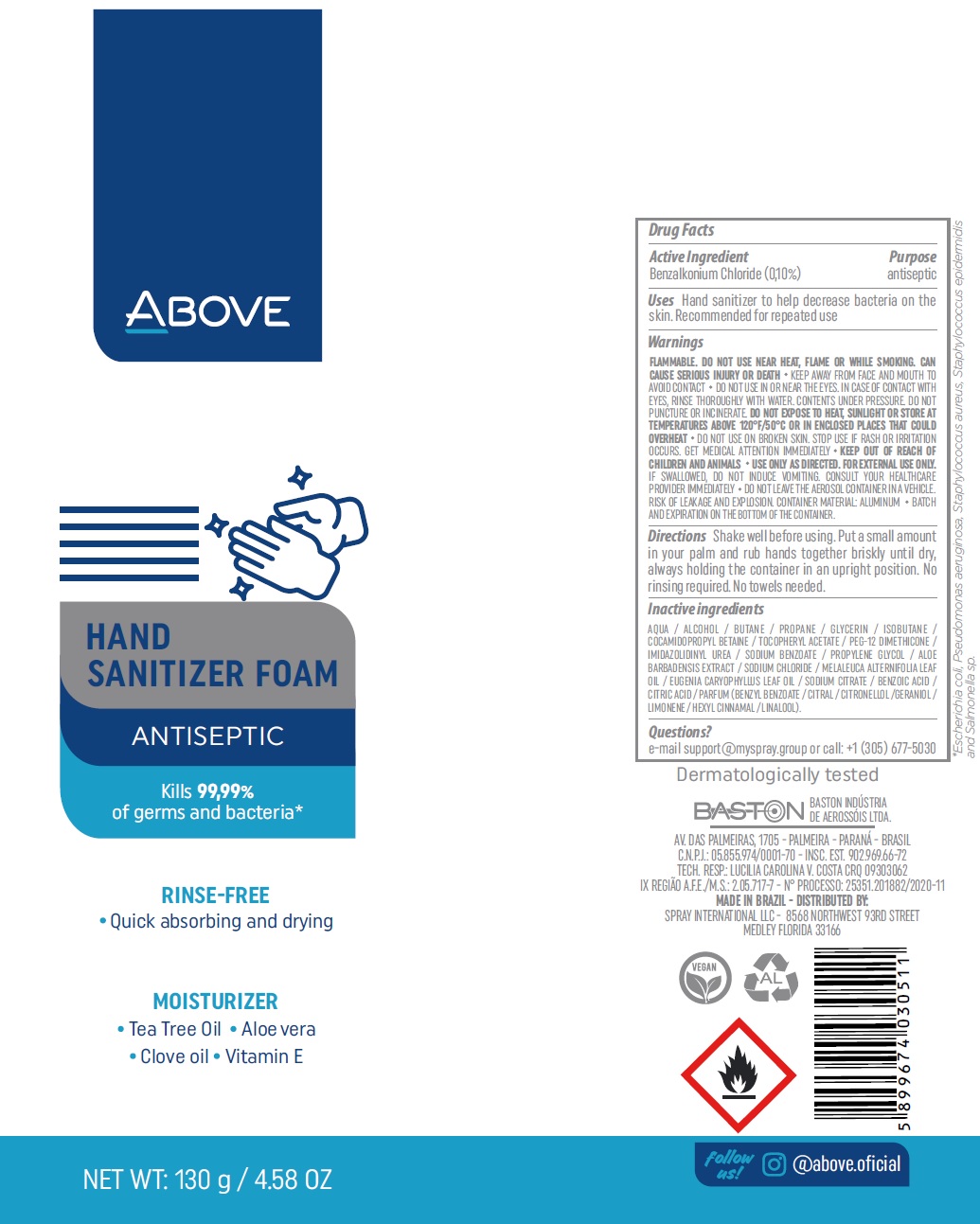 DRUG LABEL: Above Hand Sani Antiseptic
NDC: 73306-6001 | Form: AEROSOL, FOAM
Manufacturer: Baston Industria De Aerossols Ltda
Category: otc | Type: HUMAN OTC DRUG LABEL
Date: 20200819

ACTIVE INGREDIENTS: BENZALKONIUM CHLORIDE 1 mg/1 g
INACTIVE INGREDIENTS: WATER; ALCOHOL; BUTANE; PROPANE; GLYCERIN; ISOBUTANE; COCAMIDOPROPYL BETAINE; .ALPHA.-TOCOPHEROL ACETATE; PEG-12 DIMETHICONE; IMIDUREA; SODIUM BENZOATE; PROPYLENE GLYCOL; SODIUM CHLORIDE; TEA TREE OIL; SODIUM CITRATE; BENZOIC ACID; CITRIC ACID MONOHYDRATE; BENZYL BENZOATE; CITRAL; .BETA.-CITRONELLOL, (R)-; GERANIOL; LIMONENE, (+)-; .ALPHA.-HEXYLCINNAMALDEHYDE; LINALOOL, (+/-)-

Above Hand Sani Antiseptic

Active Ingredient

Benzalkonium Chloride (0,10%)

Purpose

antiseptic

Uses

Hand sanitizer to help decrease bacteria on the skin. Recommended for repeated use

Warnings

FLAMMABLE. DO NOT USE NEAR HEAT, FLAME OR WHILE SMOKING. CAN CAUSE SERIOUS INJURY OR DEATH

- KEEP AWAY FROM FACE AND MOUTH TO AVOID CONTACT

DO NOT USE

IN OR NEAR THE EYES. IN CASE OF CONTACT WITH EYES, RINSE THOROUGHLY WITH WATER. CONTENTS UNDER PRESSURE. DO NOT
PUNCTURE OR INCINERATE. DO NOT EXPOSE TO HEAT, SUNLIGHT OR STORE AT TEMPERATURES ABOVE 120°F/50°C OR IN ENCLOSED PLACES THAT COULD OVERHEAT

- DO NOT USE ON BROKEN SKIN.

STOP USE IF

RASH OR IRRITATION OCCURS. GET MEDICAL ATTENTION IMMEDIATELY

KEEP OUT OF REACH OF CHILDREN

AND ANIMALS USE ONLY AS DIRECTED. FOR EXTERNAL USE ONLY. IF SWALLOWED, DO NOT INDUCE VOMITING. CONSULT YOUR HEALTHCARE PROVIDER IMMEDIATELY DO NOT LEAVE THE AEROSOL CONTAINER IN A VEHICLE. RISK OF LEAKAGE AND EXPLOSION. CONTAINER MATERIAL: ALUMINUM BATCH AND EXPIRATION ON THE BOTTOM OF THE CONTAINER.

Directions

Shake well before using. Put a small amount in your palm and rub hands together briskly until dry, always holding the container in an upright position. No rinsing required. No towels needed.

Inactive ingredients

AQUA / ALCOHOL / BUTANE / PROPANE / GLYCERIN / ISOBUTANE / COCAMIDOPROPYL BETAINE / TOCOPHERYL ACETATE / PEG-12 DIMETHICONE / IMIDAZOLIDINYL UREA / SODIUM BENZOATE / PROPYLENE GLYCOL / ALOE BARBADENSIS EXTRACT / SODIUM CHLORIDE / MELALEUCA ALTERNIFOLIA LEAF OIL / EUGENIA CARYOPHYLLUS LEAF OIL / SODIUM CITRATE / BENZOIC ACID / CITRIC ACID / PARFUM (BENZYL BENZOATE / CITRAL / CITRONELLOL /GERANIOL / LIMONENE / HEXYL CINNAMAL / LINALOOL).

Questions?

e-mail support@myspray.group or call: +1 (305) 677-5030